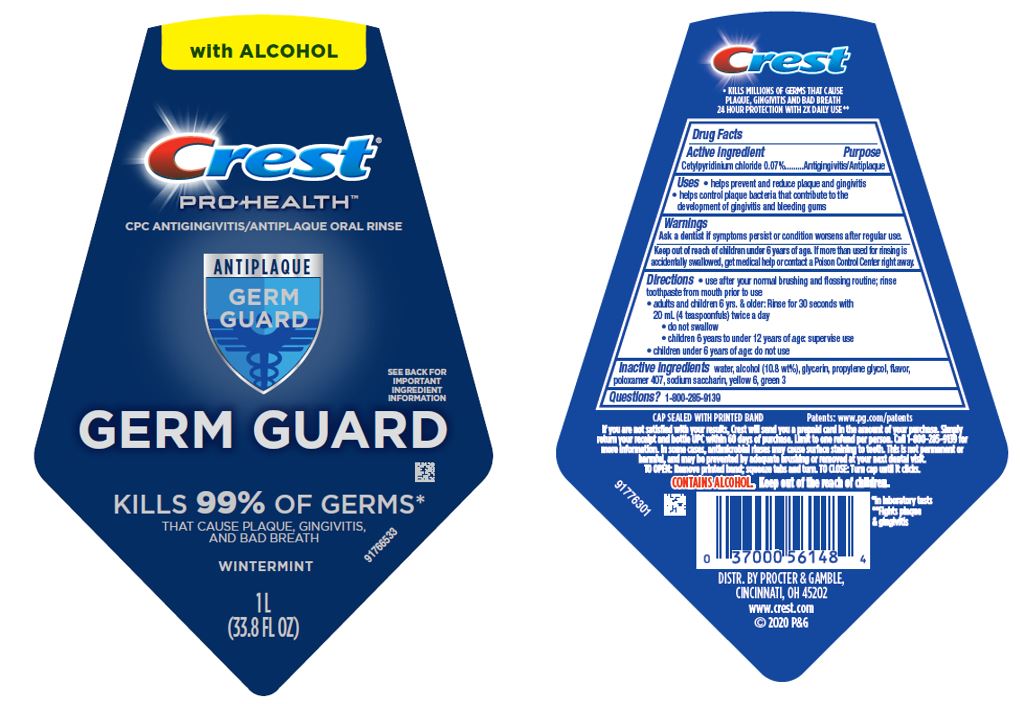 DRUG LABEL: Crest Pro-Health
NDC: 69423-939 | Form: RINSE
Manufacturer: The Procter & Gamble Manufacturing Company
Category: otc | Type: HUMAN OTC DRUG LABEL
Date: 20250806

ACTIVE INGREDIENTS: CETYLPYRIDINIUM CHLORIDE 0.014 g/1 mL
INACTIVE INGREDIENTS: WATER; ALCOHOL; GLYCERIN; PROPYLENE GLYCOL; POLOXAMER 407; SACCHARIN SODIUM; FD&C YELLOW NO. 6; FD&C GREEN NO. 3

Crest Pro Health Germ Guard

Drug Facts

Active ingredient

Cetylpyridinium chloride 0.07%

Purpose

Antigingivitis/Antiplaque

Uses

- helps prevent and reduce plaque and gingivitis
- helps control plaque bacteria that contribute to the development of gingivitis and bleeding gums

Warnings

ASK DOCTOR

Ask a dentist if symptoms persist or condition worsens after regular use.

Keep out of reach of children under 6 years of age. If more than used for rinsing is accidentally swallowed, get medical help or contact a Poison Control Center right away.

Directions

- use after your normal brushing and flossing routine; rinse toothpaste from mouth prior to use
- adults and children 6 yrs. & older: Rinse for 30 seconds with 20 mL (4 teaspoonfuls) twice a day
  - do not swallow
  - children 6 years to under 12 years of age: supervise use
- children under 6 years of age: do not use

Inactive ingredients

water, alcohol (10.8 wt%), glycerin, propylene glycol, flavor, poloxamer 407, sodium saccharin, yellow 6, green 3

Questions?

1–800–285–9139

PRINCIPAL DISPLAY PANEL - 1 L Bottle Label

with ALCOHOL

Crest®
PRO-HEALTH™
CPC ANTIGINGIVITIS/ANTIPLAQUE ORAL RINSE

ANTIPLAQUE GERM GUARD

SEE BACK LABEL FOR IMPORTANT INGREDIENT INFORMATION

GERM GUARD

KILLS 99% OF GERMS*

THAT CAUSE PLAQUE, GINGIVITIS AND BAD BREATH

WINTERMINT

1 L (33.8 FL OZ)